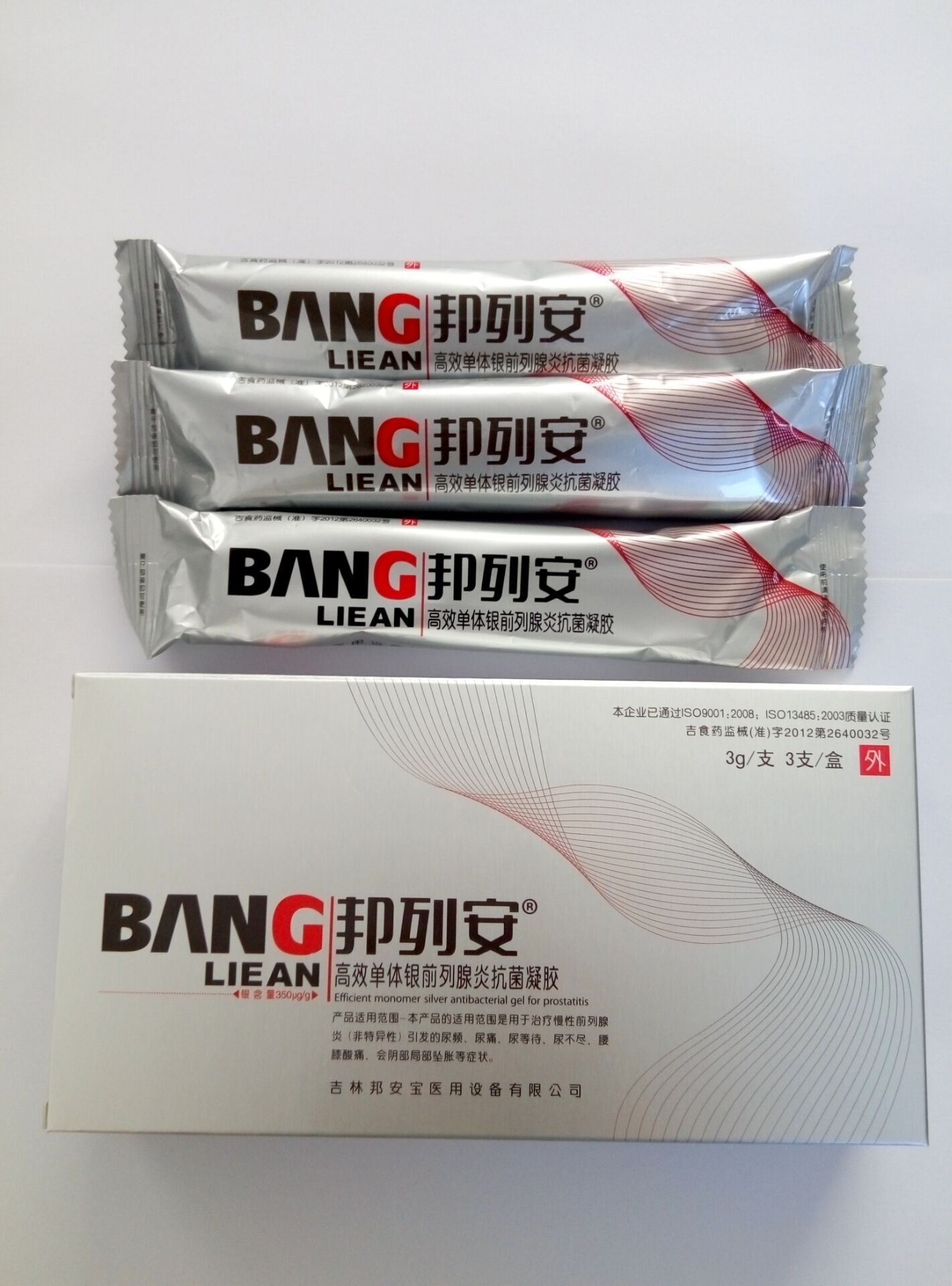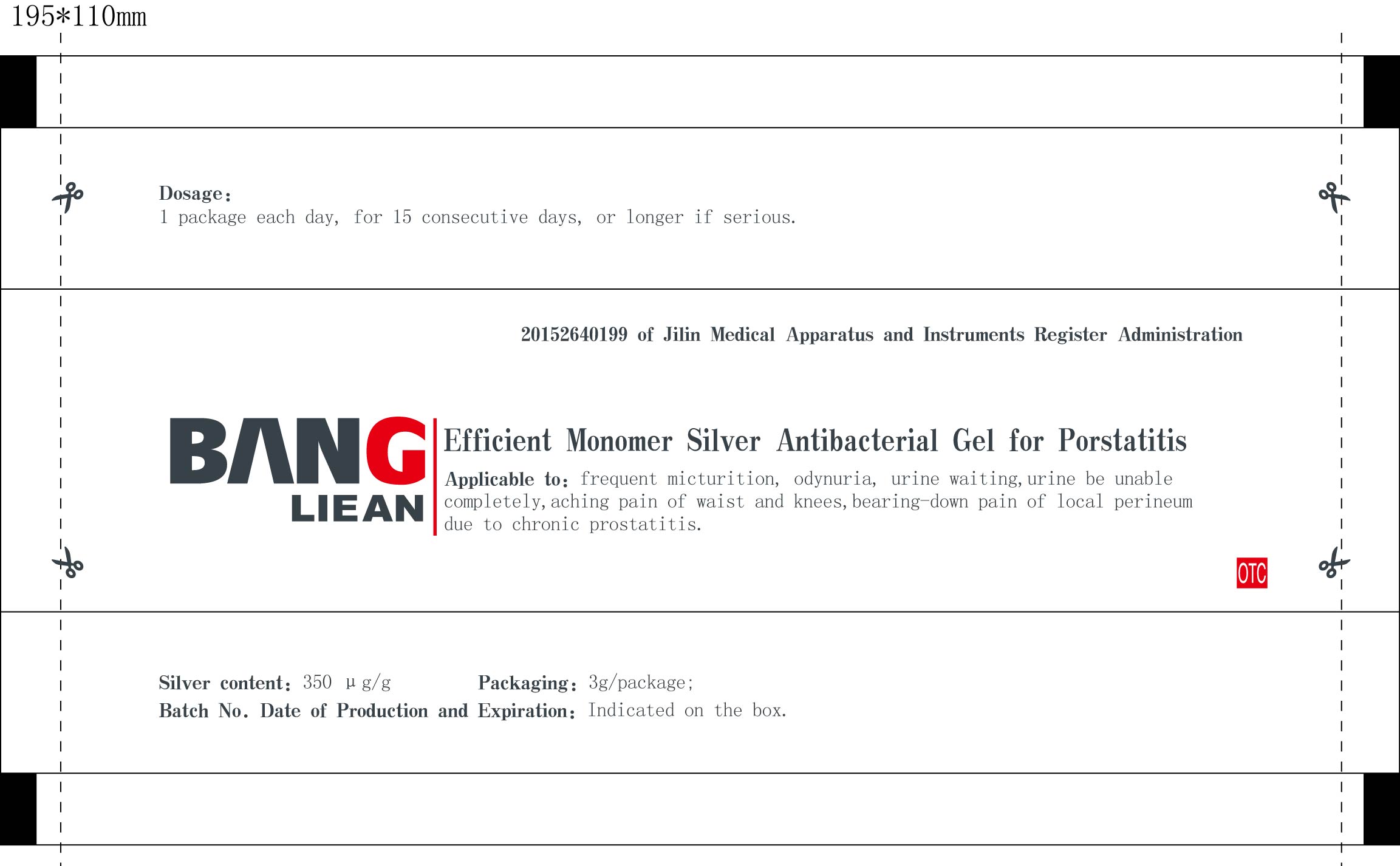 DRUG LABEL: Bang Lie An High-Efficiency Anti-Bacteria Monomer Silver Gel for Prostatitis
NDC: 60659-0201 | Form: GEL, DENTIFRICE
Manufacturer: Bang An Bao Medical Equipment Co., Ltd.
Category: homeopathic | Type: HUMAN OTC DRUG LABEL
Date: 20160108

ACTIVE INGREDIENTS: SILVER 1050 ug/3 g; WATER 2980950 ug/3 g
INACTIVE INGREDIENTS: CARBOMER 934 18000 uL/3 g

Active ingredient

Silver content: 350 μg/g; 1050 μg/package

Purpose

Frequent micturition, odynuria, urine waiting, urine be unable completely, aching pain of waist and knees, bearing-down pain of local perineum due to chronic prostatitis.

Indications and usage

Indication to bacterial diseases; and frequent micturition, odynuria, urine waiting, urine be unable completely, aching pain of waist and knees, bearing-down pain of local perineum due to chronic prostatitis.
Topical use: Apply in the rectum.

Dosage

One package each day, for 15 consecutive days, or longer if serious.

Warnings

Contraindications:
1, For external use only.
2, Do not use if allergic to silver.
Notes:
1, Do not use if package is broken; do not use with medicine that contains Vaseline, chlorine, iodine or hydrogen peroxide.
2, This product is for external use only; do not take in. The gel may change in color, which is normal and has no impact on its effects.
3, Keep away from clothes to prevent contamination.

Out of children

Keep out of reach of children. If the product is swallowed, get medical help or contact a Poison Control Center right away.

Inactive ingredient

Carbomer 934 content: 6 mg/g; 18 mg/package; 54 mg/box
Water: 993650 μg/g; 2980950 μg/package; 8942850 mg/box

Label

Label of package

Label of carton